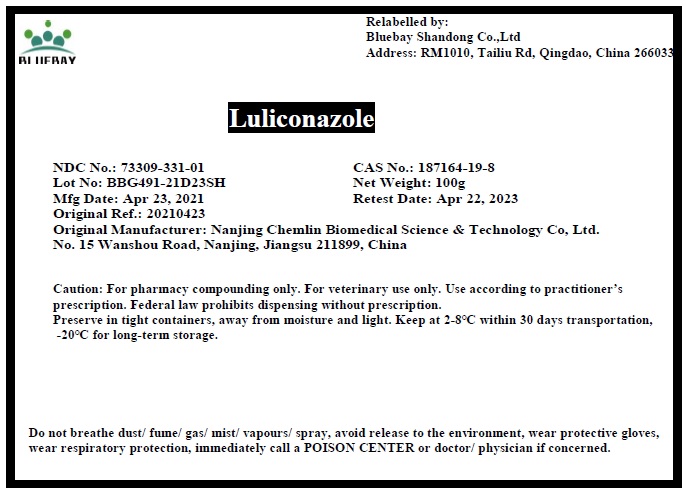 DRUG LABEL: Luliconazole
NDC: 73309-331 | Form: POWDER
Manufacturer: BLUEBAY SHANDONG CO.,LTD
Category: other | Type: BULK INGREDIENT
Date: 20210913

ACTIVE INGREDIENTS: LULICONAZOLE 1 g/1 g

Luliconazole